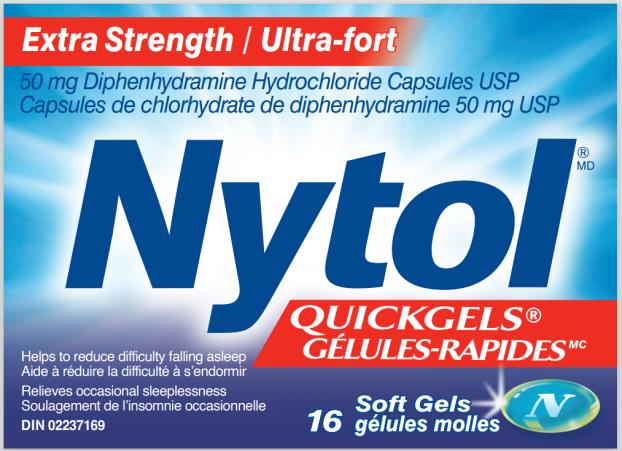 DRUG LABEL: Nytol
NDC: 63029-928 | Form: CAPSULE, GELATIN COATED
Manufacturer: Medtech Products Inc.
Category: otc | Type: HUMAN OTC DRUG LABEL
Date: 20240119

ACTIVE INGREDIENTS: DIPHENHYDRAMINE HYDROCHLORIDE 50 mg/1 1
INACTIVE INGREDIENTS: FD&C BLUE NO. 1 ALUMINUM LAKE; GELATIN; GLYCERIN; POLYETHYLENE GLYCOL, UNSPECIFIED; SORBITAN; SORBITOL; WATER

Nytol Gelcap 50 mg_Export only 63029-928

Drug Facts

Purpose

Diphenhydramine Hydrochloride 50 mg Nighttime sleep aid

Uses/ Indications

● helps to reduce difficulty falling asleep

● relieves occasional sleeplessness

Warnings

Do not use

- if you are elderly, as this drug may cause excitation rather than sedation
- with any other product containing diphenhydramine, even one used on skin
- in children under 12 years of age

Ask a doctor or pharmacist before use if you

- have
  • a breathing problem such as emphysema or chronic bronchitis
  • glaucoma
- difficulty urinating
- take sedatives or tranquilizers
- are pregnant or breast-feeding

When using this product

avoid drinking alcohol

Stop use and ask a doctor if

sleeplessness continues for more than 2 weeks. Sleeplessness may be a symptom of a serious underlying medical illness.

Keep out of reach of children.

In case of overdose, call a poison control centre or get medical help right away.

Directions

Adults and children 12 years and over:

take 1 capsule at bedtime if needed, or as directed by a doctor

- if you feel drowsy in the morning, consult a doctor or pharmacist, as you may require a lower dosage (25 mg)
- do not take more than directed

Other information

Store between 15 & 30 °C

Inactive ingredients

edible white ink, FD&C blue #1, gelatin, glycerin, polyethylene glycol, purified water, sorbitol sorbitan

Questions?

1-800-465-8811 www.nytol.ca

PRINCIPAL DISPLAY PANEL

Extra Strength Ultra-fort

Nytol®/MD

QUICKGELS®

GÉLULES-RAPIDESMC

Extra Strength Ultra-fort

50 mg Diphenhydramine Hydrochloride Capsules USP

Capsules de chlorhydrate de diphenhydramine 50 mg USP

16 soft gels

gélules molles

DIN 02237169